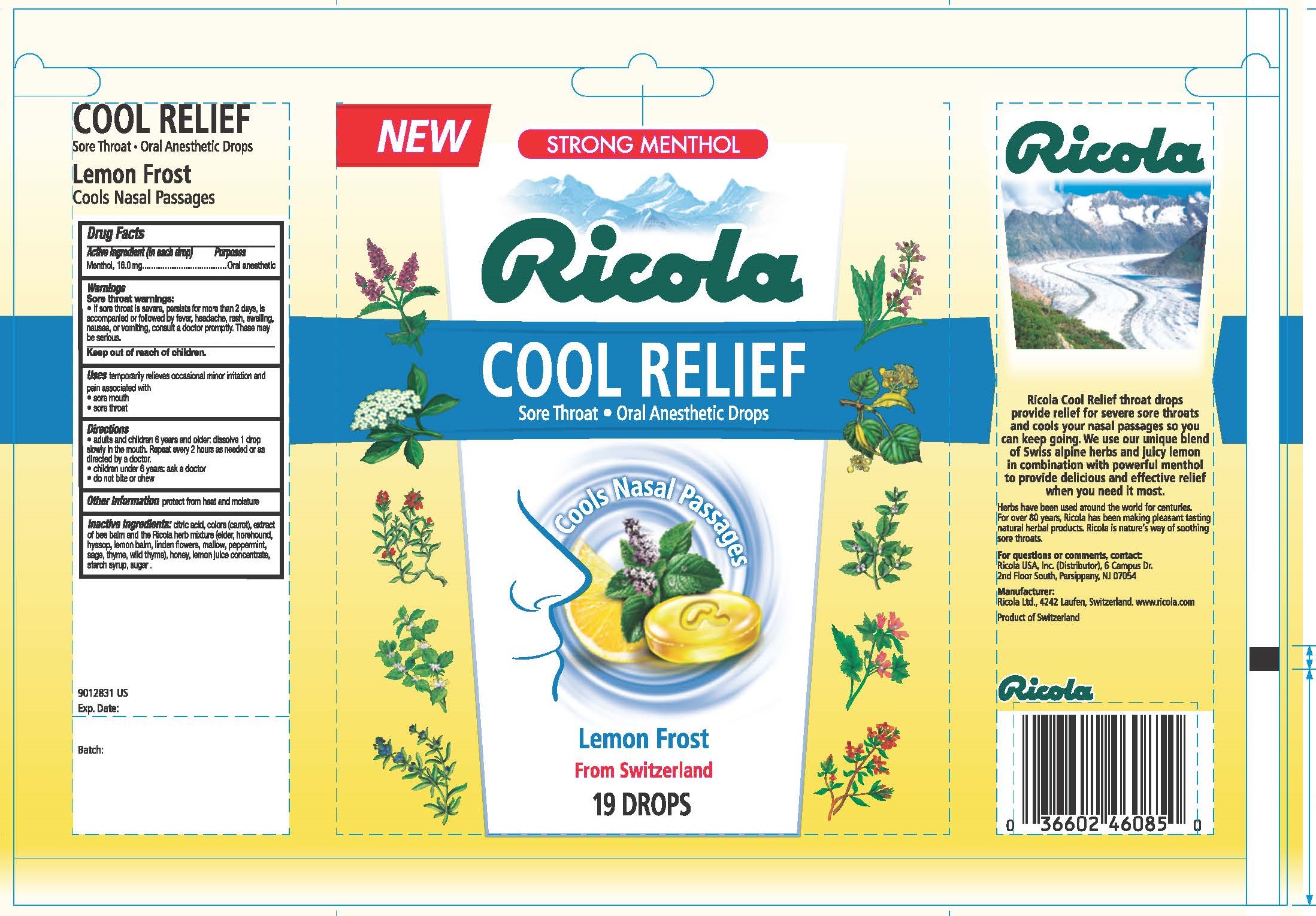 DRUG LABEL: COOL RELIEF LEMON FROST ORAL ANESTHETIC
NDC: 63667-156 | Form: LOZENGE
Manufacturer: Ricola USA Inc.
Category: otc | Type: HUMAN OTC DRUG LABEL
Date: 20241210

ACTIVE INGREDIENTS: MENTHOL 16.0 mg/1 1
INACTIVE INGREDIENTS: SUCROSE; LEMON JUICE; HONEY

COOL RELIEF LEMON FROST ORAL ANESTHETIC

Drug Facts

Purpose

Oral anesthetic

Active Ingredient (in each drop)

Menthol, 16.0 mg

Uses

temporarily relieves occasional minor irritation and pain associated with:

- sore mouth
- sore throat

Warnings

Sore throat warnings:

- if sore throat is severe, persists for more than 2 days, is accompanied or followed by fever, headache, rash, swelling, nausea, or vomiting, consult a doctor promptly. These may be serious.

Directions

- adults and children 6 years and older: dissolve 1 drop slowly in the mouth. Repeat every 2 hours as needed or as directed by a doctor
- children under 6 years: ask a doctor
- do not bite or chew

Other Information

protect from heat and moisture

Inactive Ingredients

citric acid, colors (carrot), extract of bee balm and the Ricola herb mixture (elder, horehound, hyssop, lemon balm, linden flowers, mallow, peppermint, sage, thyme, wild thyme), honey, lemon juice concentrate, starch syrup, sugar